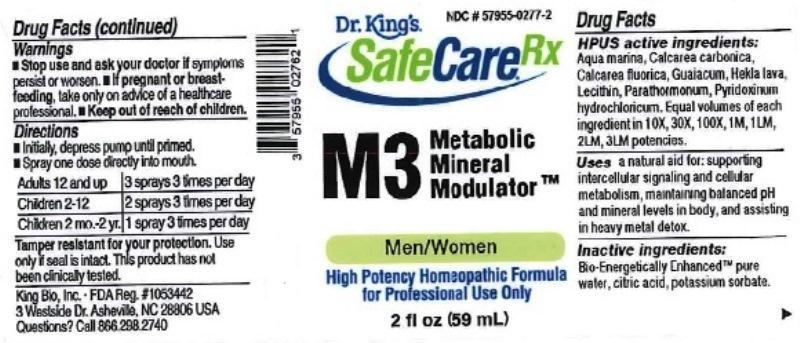 DRUG LABEL: M3 Metabolic Mineral Modulator
NDC: 57955-0277 | Form: LIQUID
Manufacturer: King Bio Inc.
Category: homeopathic | Type: HUMAN OTC DRUG LABEL
Date: 20170214

ACTIVE INGREDIENTS: SODIUM CHLORIDE 10 [hp_X]/59 mL; OYSTER SHELL CALCIUM CARBONATE, CRUDE 10 [hp_X]/59 mL; CALCIUM FLUORIDE 10 [hp_X]/59 mL; GUAIAC 10 [hp_X]/59 mL; HEKLA LAVA 10 [hp_X]/59 mL; EGG PHOSPHOLIPIDS 10 [hp_X]/59 mL; PARATHYROID HORMONE 10 [hp_X]/59 mL; PYRIDOXINE HYDROCHLORIDE 10 [hp_X]/59 mL
INACTIVE INGREDIENTS: WATER; POTASSIUM SORBATE; ANHYDROUS CITRIC ACID

M3 Metabolic Mineral Modulator

Drug Facts

___________________________________________________________________________________________________________________

HPUS active ingredients: Aqua marina, Calcarea carbonica, Calcarea fluorica, Guaiacum, Hekla lava, Lecithin, Parathormonum, Pyridoxinum hydrochloricum. Equal volumes of each ingredient in 10X, 30X, 100X, 1M, 1LM, 2LM, 3LM potencies.

INDICATIONS AND USAGE

Uses a natural aid for: supporting intercellular signaling and cellular metabolism, maintaining balanced pH and mineral levels in body, and assisting in heavy metal detox.

INACTIVE INGREDIENT

Inactive ingredients: Bio-Energetically Enhanced™ pure water, citric acid, potassium sorbate.

Warnings

- Stop use and ask your doctor if symptoms persist or worsen.
- If pregnant or breast-feeding, take only on advice of a healthcare professional.

- Keep out of reach of children.

Directions

- Initially, depress pump until primed.
- Spray one dose directly into mouth.
- Adults: 3 sprays 3 times per day.
- Children (2-12 years): 2 sprays 3 times per day.
- Children (1 month-2 years): 1 spray 3 times per day.

OTHER SAFETY INFORMATION

Tamper resistant for your protection. Use only if safety seal is intact. This product has not been clinically tested.

PURPOSE

Uses a natural aid for:

- supporting intercellular signaling
- cellular metabolism
- maintaining balanced pH
- mineral levels in body
- assisting in heavy metal detox